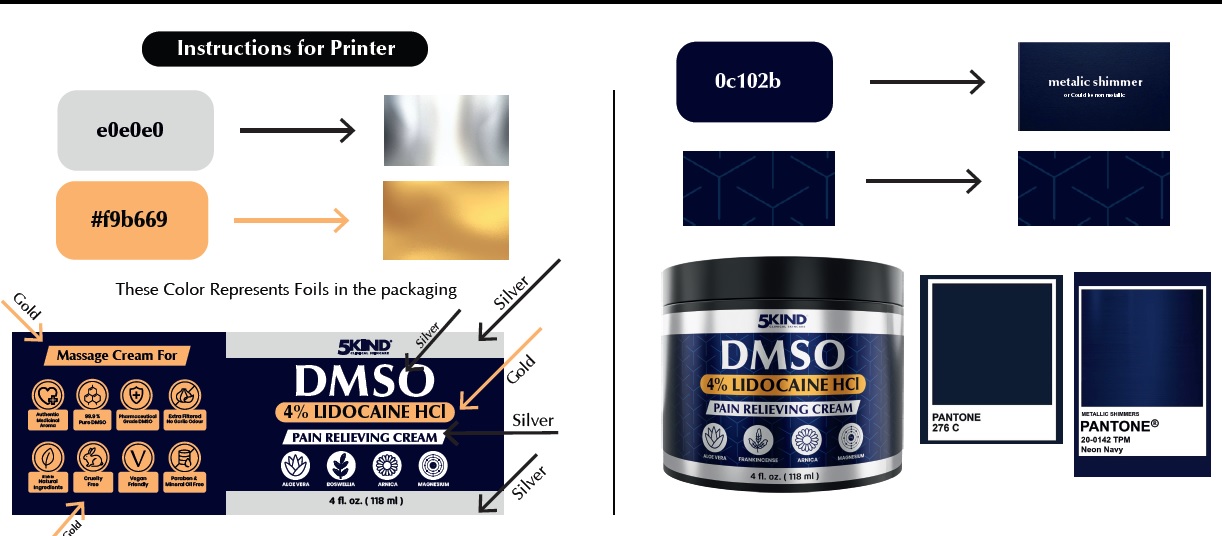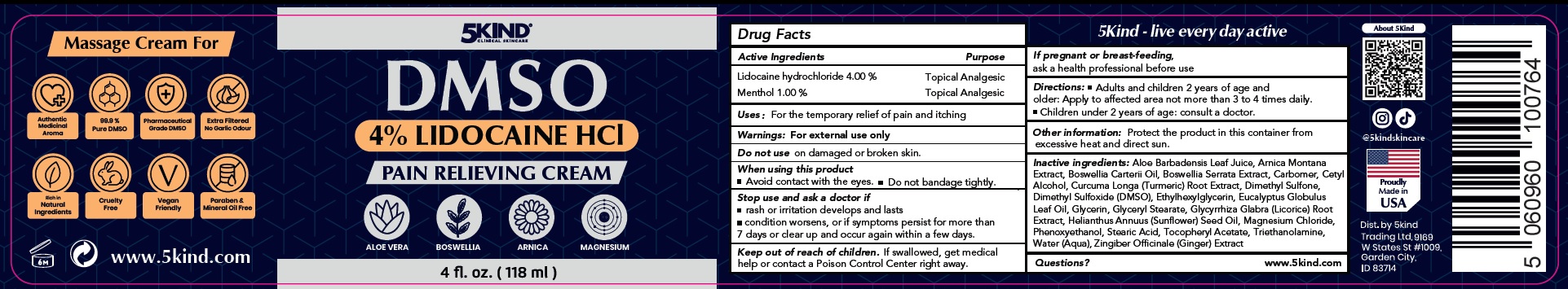 DRUG LABEL: 5Kind DMSO 4 Lidocaine HCl Pain Relieving
NDC: 85978-929 | Form: CREAM
Manufacturer: 5KIND TRADING LTD
Category: otc | Type: HUMAN OTC DRUG LABEL
Date: 20260225

ACTIVE INGREDIENTS: LIDOCAINE HYDROCHLORIDE 40 mg/1 mL; MENTHOL 10 mg/1 mL
INACTIVE INGREDIENTS: ALOE VERA LEAF JUICE; ARNICA MONTANA WHOLE; FRANKINCENSE OIL; INDIAN FRANKINCENSE; CARBOMER HOMOPOLYMER, UNSPECIFIED TYPE; CETYL ALCOHOL; TURMERIC; DIMETHYL SULFONE; DIMETHYL SULFOXIDE; ETHYLHEXYLGLYCERIN; EUCALYPTUS OIL; GLYCERIN; GLYCERYL MONOSTEARATE; GLYCYRRHIZA GLABRA (LICORICE) ROOT POWDER; SUNFLOWER OIL; MAGNESIUM CHLORIDE; PHENOXYETHANOL; STEARIC ACID; .ALPHA.-TOCOPHEROL ACETATE; TROLAMINE; WATER; GINGER

5Kind DMSO 4% Lidocaine HCl Pain Relieving Cream

Active Ingredients

Lidocaine hydrochloride 4.00 %
Menthol 1.00 %

Purpose

Topical Analgesic

Uses :

For the temporary relief of pain and itching

Warnings:

For external use only

Do not use

on damaged or broken skin.

When using this product

- Avoid contact with the eyes.
- Do not bandage tightly.

Stop use and ask a doctor if

- rash or irritation develops and lasts
- condition worsens, or if symptoms persist for more than 7 days or clear up and occur again within a few days.

Keep out of reach of children.

If swallowed, get medical help or contact a Poison Control Center right away.

If preg nant or breast-feeding,

ask a health professional before use

Directions:

- Adults and children 2 years of age and older: Apply to affected area not more than 3 to 4 times daily.
- Children under 2 years of age: consult a doctor.

Other information:

Protect the product in this container from excessive heat and direct sun.

Inactive ingredients:

Aloe Barbadensis Leaf Juice, Arnica Montana Extract, Boswellia Carterii Oil, Boswellia Serrata Extract, Carbomer, Cetyl Alcohol, Curcuma Longa (Turmeric) Root Extract, Dimethyl Sulfone, Dimethyl Sulfoxide (DMSO), Ethylhexylglycerin, Eucalyptus Globulus Leaf Oil, Glycerin, Glyceryl Stearate, Glycyrrhiza Glabra (Licorice) Root Extract, Helianthus Annuus (Sunflower) Seed Oil, Magnesium Chloride, Phenoxyethanol, Stearic Acid, Tocopheryl Acetate, Triethanolamine, Water (Aqua), Zingiber Officinale (Ginger) Extract

Questions?

www.5kind.com